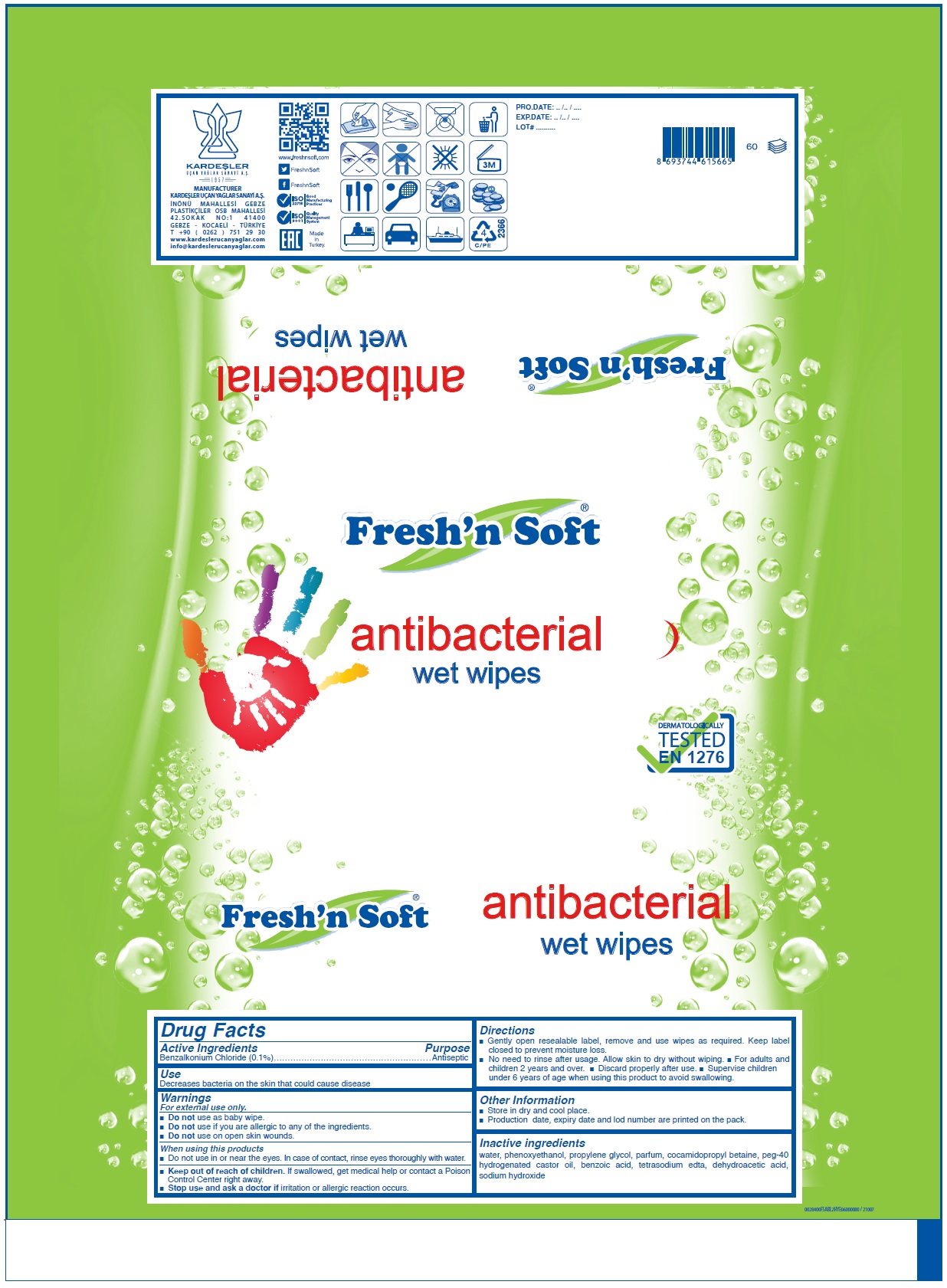 DRUG LABEL: FRESH N SOFT ANTIBACTERIAL WET WIPES
NDC: 86937-005 | Form: CLOTH
Manufacturer: KARDESLER UCAN YAGLAR SANAYI ANONIM SIRKETI
Category: otc | Type: HUMAN OTC DRUG LABEL
Date: 20201223

ACTIVE INGREDIENTS: BENZALKONIUM CHLORIDE 0.1 g/100 g
INACTIVE INGREDIENTS: WATER; PHENOXYETHANOL; PROPYLENE GLYCOL; COCAMIDOPROPYL BETAINE; POLYOXYL 40 HYDROGENATED CASTOR OIL; BENZOIC ACID; EDETATE SODIUM; DEHYDROACETIC ACID; SODIUM HYDROXIDE

Fresh'n Soft® antibacterial wet wipes

Active Ingredients

Benzalkonium Chloride (0.1%)

Purpose

Antiseptic

Use

Decreases bacteria on the skin that could cause disease

Warnings

For external use only.

• Do not use as baby wipe.

• Do not use if you are allergic to any of the ingredients.

• Do not use on open skin wounds.

When using this products

• Do not use in or near the eyes. In case of contact, rinse eyes thoroughly with water.

• Stop use and ask a doctor if irritation or allergic reaction occurs.

• Keep out of reach of children. If swallowed, get medical help or contact a Poison Control Center right away.

Directions

• Gently open resealable label, remove and use wipes as required. Keep label closed to prevent moisture loss.

• No need to rinse after usage. Allow skin to dry without wiping. • For adults and children 2 years and over. • Discard properly after use. • Supervise children under 6 years of age when using this product to avoid swallowing.

Other Information

• Store in dry and cool place.
• Production date, expiry date and lot number are printed on the pack.

Inactive ingredients

water, phenoxyethanol, propylene glycol, parfum, cocamidopropyl betaine, peg-40 hydrogenated castor oil, benzoic acid, tetrasodium edta, dehydroacetic acid, sodium hydroxide

DERMATOLOGICALLY TESTED

EN 1276

KARDESLER

UCAN YAGLAR SANAYI A.S.

1957

MANUFACTURER
KARDESLER UÇAN YAGLAR SANAYI A.S.

INÖNÜ MAHALLESI GEBZE
PLASTIKÇILER OSB MAHALLESI
42.SOKAK NO:1 41400
GEBZE - KOCAELI - TÜRKIYE
T +90 (0262) 751 29 30
www.kardeslerucanyaglar.com
info@kardeslerucanyaglar.com
www.freshnsoft.com

FreshnSoft

FreshnSoft

ISO 22716 Good Manufacturing Practices

ISO 9001 Quality Management System

EAC Made in Turkey.